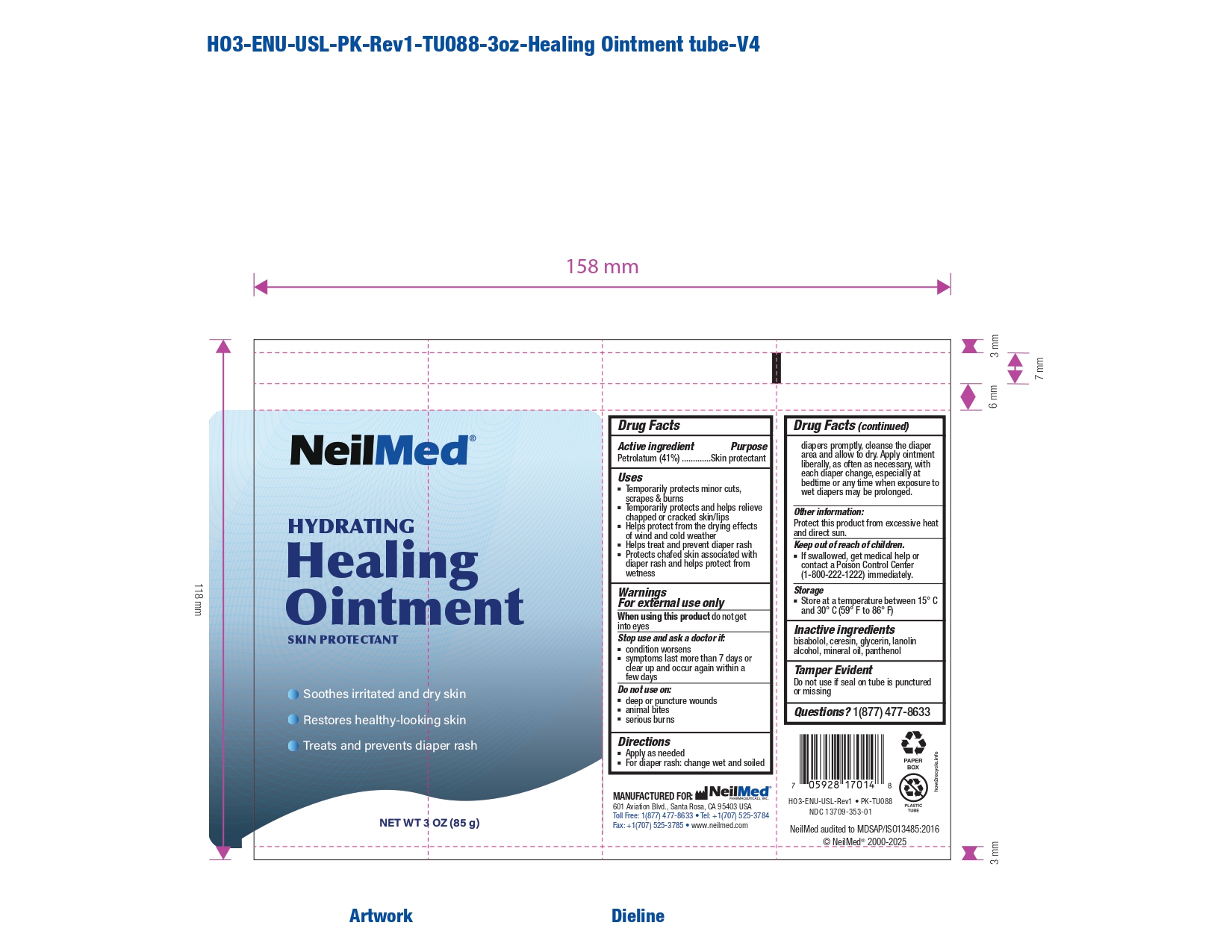 DRUG LABEL: Hydrating Healing
NDC: 13709-353 | Form: OINTMENT
Manufacturer: Neilmed Pharmaceuticals Inc.,
Category: otc | Type: HUMAN OTC DRUG LABEL
Date: 20251228

ACTIVE INGREDIENTS: PETROLATUM 410 mg/1 g
INACTIVE INGREDIENTS: CERESIN; GLYCERIN; MINERAL OIL; BISABOLOL; LANOLIN ALCOHOL; PANTHENOL

Healing Ointment

Drug Facts

Active ingredient

Petrolatum (41%).....

Purpose

Skin protectant

Uses

- Temporarily protects minor cuts, scrapes & burns
- Temporarily protects and helps relieve chapped or cracked skin/lips
- Helps protect from the drying effects of wind and cold weather
- Helps treat and prevent diaper rash
- Protects chafed skin associated with diaper rash and helps protect from wetness

Warnings

For external use only

When using this product

do not get into eyes

Stop use and ask a doctor if:

- condition worsens
- symptoms last more than 7 days or clear up and occur again within a few days

Do not use on:

- deep or puncture wounds
- animal bites
- serious burns

Directions

- Apply as needed
- For diaper rash: change wet and soiled diapers promptly, cleanse the diaper area and allow to dry. Apply ointment liberally, as often as necessary, with each diaper change, especially at bedtime or any time when exposure to wet diapers may be prolonged.

Other information:

Protect this product from excessive heat and direct sun.

Keep out of reach of children.

- If swallowed, get medical help or contact a Poison Control Center (1-800-222-1222) immediately.

Storage

- Store at a temperature between 15° C and 30° C (59° F to 86° F)

Inactive ingredients

- Bisabolol
- Ceresin
- Glycerin
- Lanolin alcohol
- Mineral oil
- Panthenol

Tamper Evident

Do not use if seal on tube is punctured or missing

Questions?

1(877) 477-8633